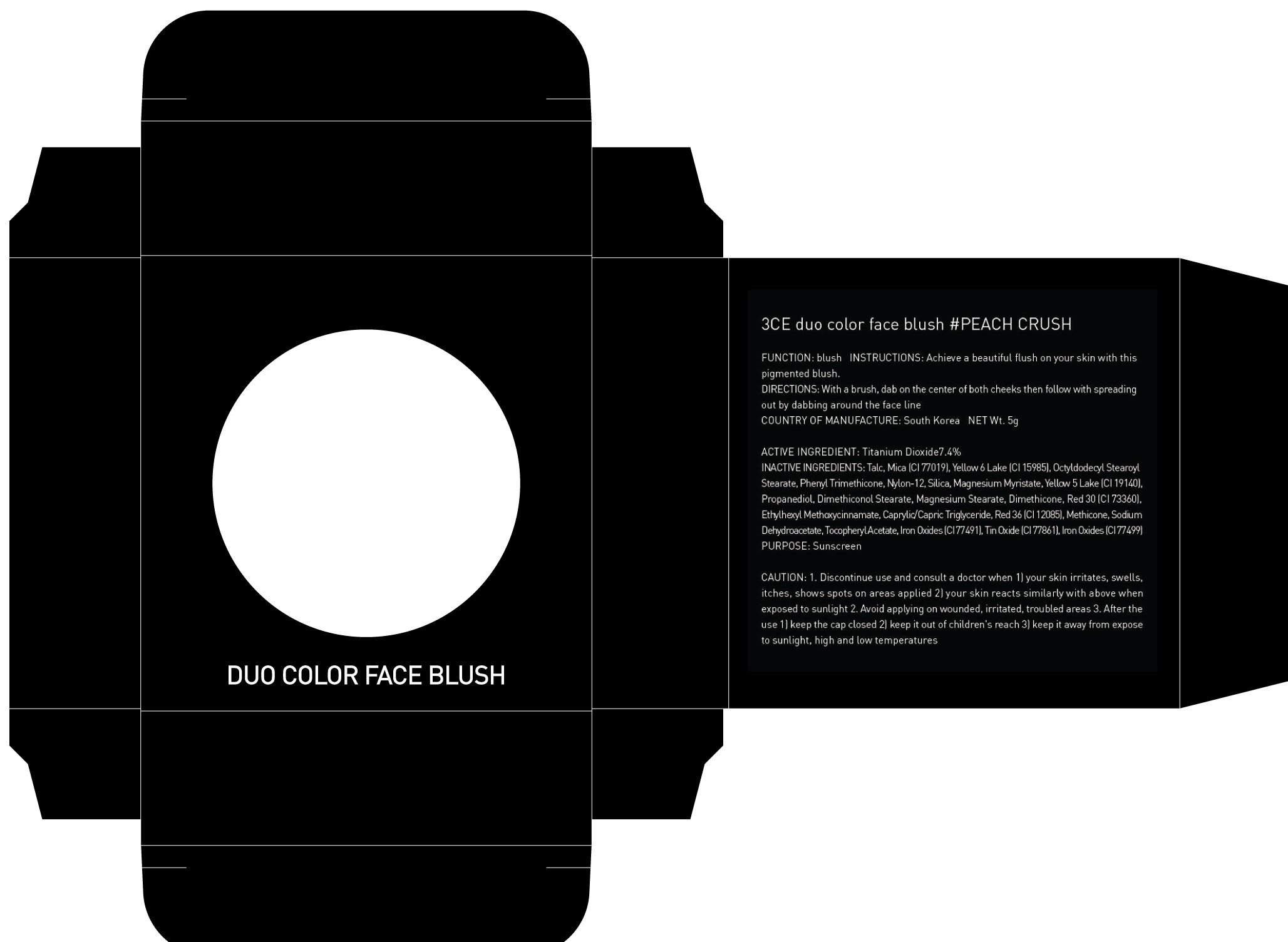 DRUG LABEL: 3CE DUO COLOR FACE BLUSH PEACH CRUSH
NDC: 60764-062 | Form: POWDER
Manufacturer: Nanda Co., Ltd
Category: otc | Type: HUMAN OTC DRUG LABEL
Date: 20161004

ACTIVE INGREDIENTS: Titanium Dioxide 0.37 g/5 g
INACTIVE INGREDIENTS: Talc; Mica

ACTIVE INGREDIENT

Active Ingredient: Titanium Dioxide 7.4%

INACTIVE INGREDIENT

Inactive Ingredients: Talc, Mica (CI 77019), Yellow 6 Lake (CI 15985), Octyldodecyl Stearoyl Stearate, Phenyl Trimethicone, Nylon-12, Silica, Magnesium Myristate, Yellow 5 Lake (CI 19140), Propanediol, Dimethiconol Stearate, Magnesium Stearate, Dimethicone, Red 30 (CI 73360), Ethylhexyl Methoxycinnamate, Caprylic/Capric Triglyceride, Red 36 (CI 12085), Methicone, Sodium Dehydroacetate, Tocopheryl Acetate, Iron Oxides (CI 77491), Tin Oxide (CI 77861), Iron Oxides (CI 77499)

PURPOSE

Purpose: Sunscreen

CAUTION

CAUTION: 1. Discontinue use and consult a doctor when - your skin irritates, swells, itches, shows spots on areas applied - your skin reacts similarly with above when exposed to sunlight 2. Avoid applying on wounded, irritated, troubled areas 3. After the use - keep the cap closed - keep it out of children's reach - keep it away from expose to sunlight, high and low temperatures

DESCRIPTION

INSTRUCTIONS: Achieve a beautiful flush on your skin with this pigmented blush.

Directions: With a brush, dab on the center of both cheeks then follow with spreading out by dabbing around the face line